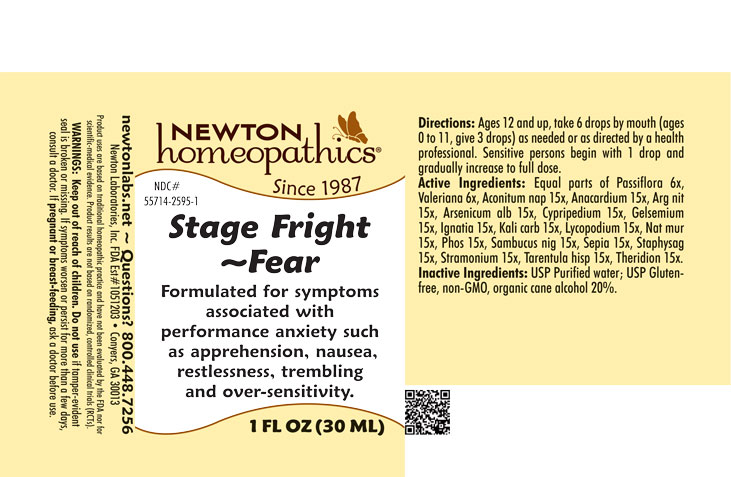 DRUG LABEL: Stage Fright-Fear
NDC: 55714-2595 | Form: LIQUID
Manufacturer: Newton Laboratories, Inc.
Category: homeopathic | Type: HUMAN OTC DRUG LABEL
Date: 20250211

ACTIVE INGREDIENTS: ACONITUM NAPELLUS 15 [hp_X]/1 mL; SEMECARPUS ANACARDIUM JUICE 15 [hp_X]/1 mL; SILVER NITRATE 15 [hp_X]/1 mL; ARSENIC TRIOXIDE 15 [hp_X]/1 mL; CYPRIPEDIUM PARVIFLORUM VAR. PUBESCENS ROOT 15 [hp_X]/1 mL; GELSEMIUM SEMPERVIRENS ROOT 15 [hp_X]/1 mL; STRYCHNOS IGNATII SEED 15 [hp_X]/1 mL; POTASSIUM CARBONATE 15 [hp_X]/1 mL; LYCOPODIUM CLAVATUM SPORE 15 [hp_X]/1 mL; SODIUM CHLORIDE 15 [hp_X]/1 mL; PHOSPHORUS 15 [hp_X]/1 mL; SAMBUCUS NIGRA FLOWERING TOP 15 [hp_X]/1 mL; SEPIA OFFICINALIS JUICE 15 [hp_X]/1 mL; DELPHINIUM STAPHISAGRIA SEED 15 [hp_X]/1 mL; DATURA STRAMONIUM 15 [hp_X]/1 mL; LYCOSA TARANTULA 15 [hp_X]/1 mL; THERIDION CURASSAVICUM 15 [hp_X]/1 mL; PASSIFLORA INCARNATA FLOWERING TOP 6 [hp_X]/1 mL; VALERIAN 6 [hp_X]/1 mL
INACTIVE INGREDIENTS: ALCOHOL; WATER

Stage 2595L

INDICATIONS & USAGE SECTION

Formulated for symptoms associated with performance anxiety such as apprehension, nausea, restlessness, trembling and over-sensitivity.

DOSAGE & ADMINISTRATION SECTION

Directions: Ages 12 and up, take 6 drops by mouth (ages 0 to 11, give 3 drops) as needed or as directed by a health professional. Sensitive persons begin with 1 drop and gradually increase to full dose.

OTC - ACTIVE INGREDIENT SECTION

Active Ingredients: Equal parts of Passiflora 6x, Valeriana 6x, Aconitum nap. 15x, Anacardium 15x, Arg. nit. 15x, Arsenicum alb. 15x, Cypripedium 15x, Gelsemium 15x, Ignatia 15x, Kali carb.15x, Lycopodium 15x, Nat. mur. 15x, Phos. 15x, Sambucus nig. 15x, Sepia 15x, Staphysag. 15x, Stramonium 15x, Tarentula hisp. 15x, Theridion 15x.

OTC - PURPOSE SECTION

Formulated for symptoms associated with performance anxiety such as apprehension, nausea, restlessness, trembling and over-sensitivity.

INACTIVE INGREDIENT SECTION

Inactive Ingredients: USP Purified Water; USP Gluten-free, non-GMO, organic cane alcohol 20%.

QUESTIONS SECTION

newtonlabs.net – Questions? 800.448.7256

Newton Laboratories, Inc. FDA Est # 1051203 - Conyers, GA 30013

WARNINGS SECTION

WARNINGS: Keep out of reach of children. Do not use if tamper-evident seal is broken or missing. If symptoms worsen or persist for more than a few days, consult a doctor. If pregnant or breast-feeding, ask a doctor before use.

OTC - PREGNANCY OR BREAST FEEDING SECTION

If pregnant or breast-feeding, ask a doctor before use.

OTC - KEEP OUT OF REACH OF CHILDREN SECTION

Keep out of reach of children.